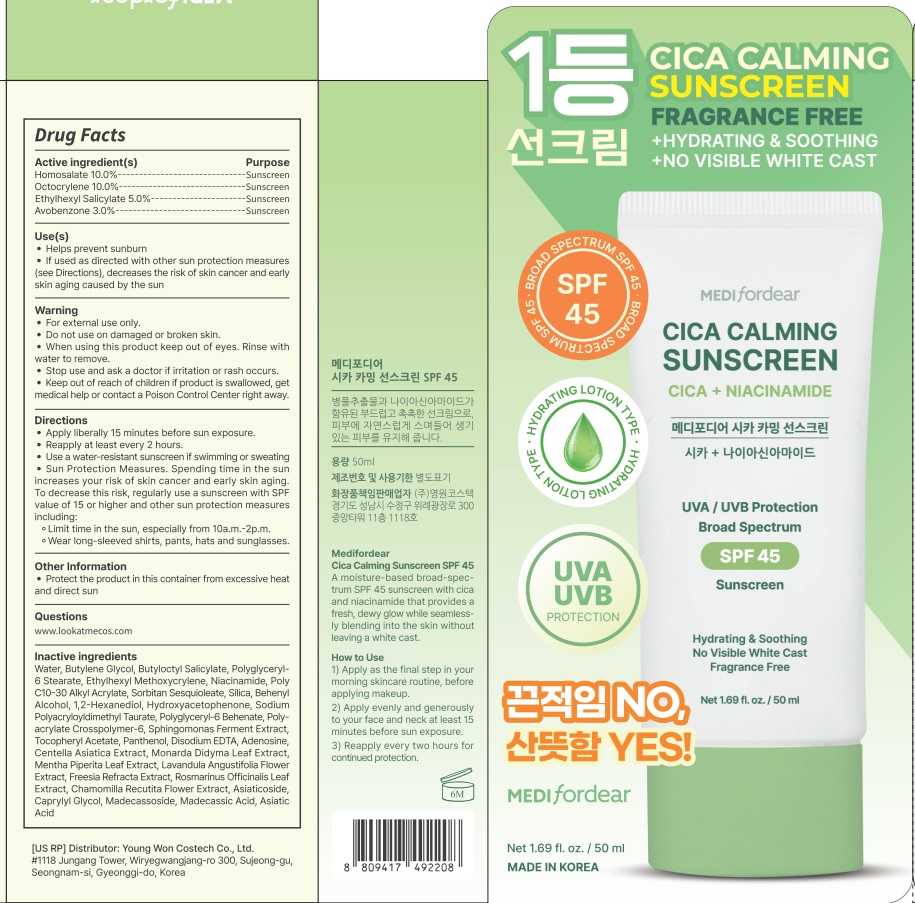 DRUG LABEL: MEDIFORDEAR CICA CALMING SUNSCREEN
NDC: 72169-550 | Form: CREAM
Manufacturer: Youngwon Costech Co.,ltd.
Category: otc | Type: HUMAN OTC DRUG LABEL
Date: 20250115

ACTIVE INGREDIENTS: HOMOSALATE 10 g/100 mL; OCTISALATE 5 g/100 mL; OCTOCRYLENE 10 g/100 mL; AVOBENZONE 3 g/100 mL
INACTIVE INGREDIENTS: POLYGLYCERYL-6 STEARATE; ETHYLHEXYL METHOXYCRYLENE; WATER; BUTYLENE GLYCOL; NIACINAMIDE; BUTYLOCTYL SALICYLATE

Active ingredient(s)

Homosalate 10.0%
Octocrylene 10.0%
Ethylhexyl Salicylate 5.0%
Avobenzone 3.0%

Purpose

Sunscreen

INDICATIONS AND USAGE

Use(s)

- Helps prevent sunburn

- If used as directed with other sun protection measures (see Directions), decreases the risk of skin cancer and early skin aging caused by the sun

Warning

- For external use only.

- Do not use on damaged or broken skin.

- When using this product keep out of eyes. Rinse with water to remove.

- Stop use and ask a doctor if irritation or rash occurs.

- Keep out of reach of children if product is swallowed, get medical help or contact a Poison Control Center right away.

Keep out of reach of children if product is swallowed, get medical help or contact a Poison Control Center right away.

Directions

- Apply liberally 15 minutes before sun exposure.

- Reapply at least every 2 hours.

- Use a water-resistant sunscreen if swimming or sweating

- Sun Protection Measures. Spending time in the sun increases your risk of skin cancer and early skin aging. To decrease this risk, regularly use a sunscreen with SPF value of 15 or higher and other sun protection measures including:

Limit time in the sun, especially from 10a.m.-2p.m.
Wear long-sleeved shirts, pants, hats and sunglasses.

Other Information

-Protect the product in this container from excessive heat and direct sun

Questions

www.lookatmecos.com

Inactive ingredients

Water, Butylene Glycol, Butyloctyl Salicylate, Polyglyceryl-6 Stearate, Ethylhexyl Methoxycrylene, Niacinamide, Poly C10-30 Alkyl Acrylate, Sorbitan Sesquioleate, Silica, Behenyl Alcohol, 1,2-Hexanediol, Hydroxyacetophenone, Sodium Polyacryloyldimethyl Taurate, Polyglyceryl-6 Behenate, Polyacrylate Crosspolymer-6, Sphingomonas Ferment Extract, Tocopheryl Acetate, Panthenol, Disodium EDTA, Adenosine, Centella Asiatica Extract, Monarda Didyma Leaf Extract, Mentha Piperita Leaf Extract, Lavandula Angustifolia Flower Extract, Freesia Refracta Extract, Rosmarinus Officinalis Leaf Extract, Chamomilla Recutita Flower Extract, Asiaticoside, Caprylyl Glycol, Madecassoside, Madecassic Acid, Asiatic Acid